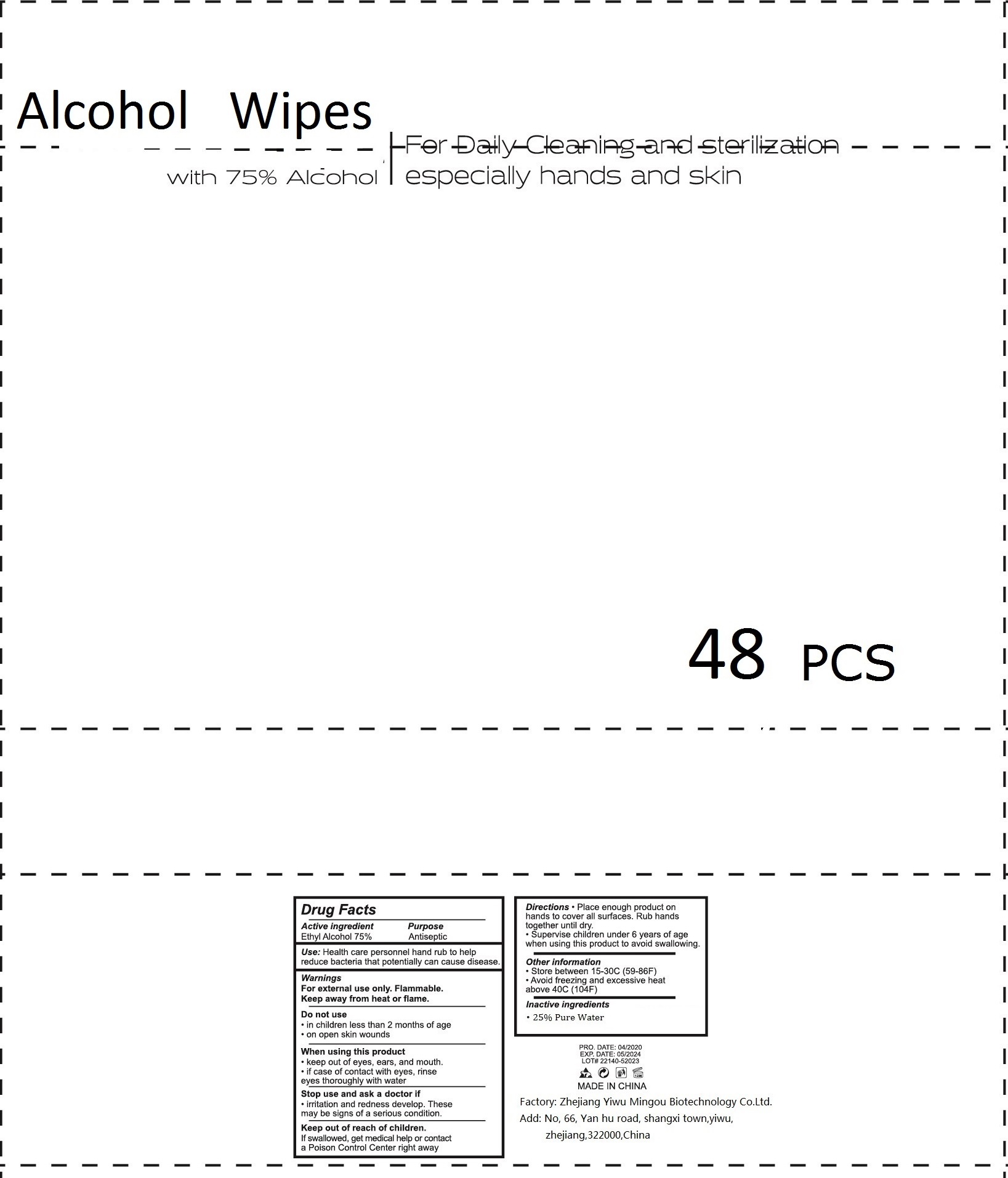 DRUG LABEL: Alcohol Wipes
NDC: 78536-003 | Form: CLOTH
Manufacturer: Zhejiang Yiwu Mingou Biotechnology Co., Ltd.
Category: otc | Type: HUMAN OTC DRUG LABEL
Date: 20200812

ACTIVE INGREDIENTS: ALCOHOL 75 mL/100 mL
INACTIVE INGREDIENTS: WATER

78536-003 75% Alcohol Wipes

ACTIVE INGREDIENT

Ethyl Alcohol 75%

PURPOSE

Antiseptic

USE

Use: Health care personnel hand rub to help
reduce bacteria that potentially can cause disease.

Warning

For external use only. Flammable.
Keep away from heat or flame.
Do not use
●in children less than 2 months of age
●on open skin wounds
When using this product
●keep out of eyes, ears, and mouth.
●if case of contact with eyes, rinse
eyes thoroughly with water
Stop use and ask a doctor if
●irritation and redness develop. These
may be signs of a serious condition.

Keep out of reach of children.
If swallowed, get medical help or contact
a Poison Control Center right away

Directions

Directions●Place enough product on
hands to cover all surfaces. Rub hands
together until dry.
●Supervise children under 6 years of age
when using this product to avoid swallowing.

Inactive ingredients

25% Pure Water